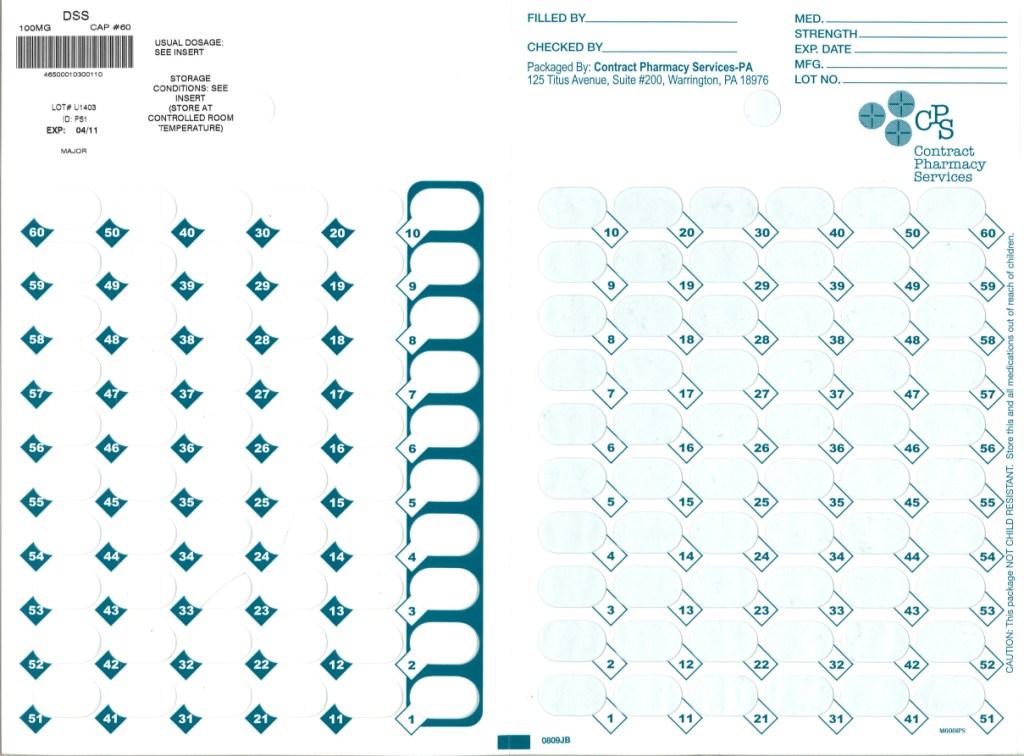 DRUG LABEL: Docusate Sodium
NDC: 67046-139 | Form: CAPSULE, LIQUID FILLED
Manufacturer: Contract Pharmacy Services-PA
Category: otc | Type: HUMAN OTC DRUG LABEL
Date: 20100730

ACTIVE INGREDIENTS: DOCUSATE SODIUM 100 mg/1 1

Docusate Sodium 100 mg

ACTIVE INGREDIENT (IN EACH CAPSULE)

Docusate sodium 100 mg

PURPOSE

Stool softener

USES

- relieves occasional constipation (irregularity)
  generally produces a bowel movement in 12 to 72 hours

WARNINGS

Do not use

- if you are presently taking mineral oil, unless told to do so by a doctor

Ask a doctor before use if you have

- stomach pain
- nausea
- vomiting
- noticed a sudden change in bowel movements that continues over a period of 2 weeks

Stop use and ask a doctor if

- you have rectal bleeding or fail to have a bowel movement after use of a laxative.
  These could be signs of a serious condition.
- you need to use a stool softener laxative for more than 1 week

If pregnant or breast-feeding,

ask a health professional before use.

Keep out of reach of children.

In case of overdose, get medical help or contact a Poison Control Center right away.

DIRECTIONS

- Take only by mouth. Doses may be taken as a single daily dose or in divided doses.
-
  adults and children 12 years and over | take 1-3 capsules daily
  children 2 to under 12 years of age | take 1 capsules daily
  children under 2 years | ask a doctor

OTHER INFORMATION

- each capsule contains: sodium 6 mg
- store at 25°C (77°F)); excursions permitted between 15°-30°C (59°-86°F)

INACTIVE INGREDIENTS

FD&C Red No. 40, FD&C Yellow No. 6, edible ink, gelatin, glycerin, polyethylene blycol, propylene glycol, purified water and sorbitol special

QUESTIONS OR COMMENTS?

Distributed by: Major Pharmaceuticals, 31778 Enterprise Drive, Livonia, MI 48150, U.S.A.

call toll free 734-743-6000

Repackaged by:
Contract Pharmacy Services-PA
125 Titus Ave Suite 200
Warrington, PA 18976 USA

Original--07/2010--NJW

Package Label

Blister of 60 Capsules